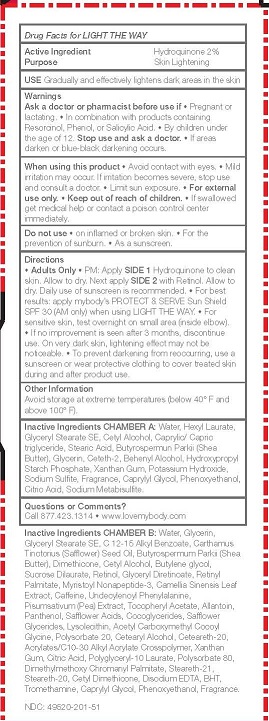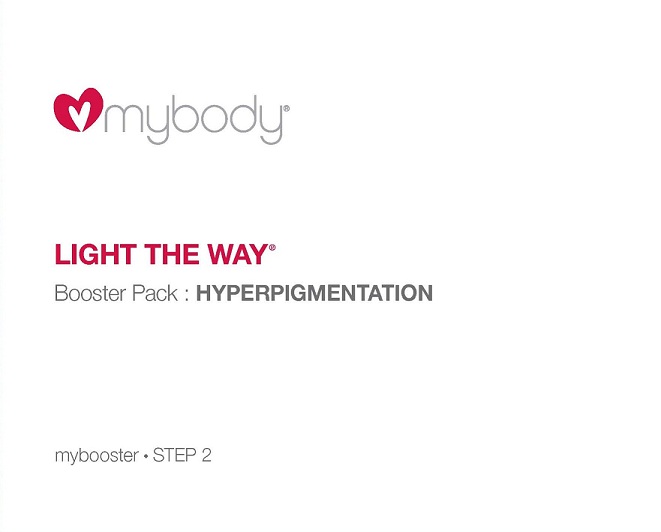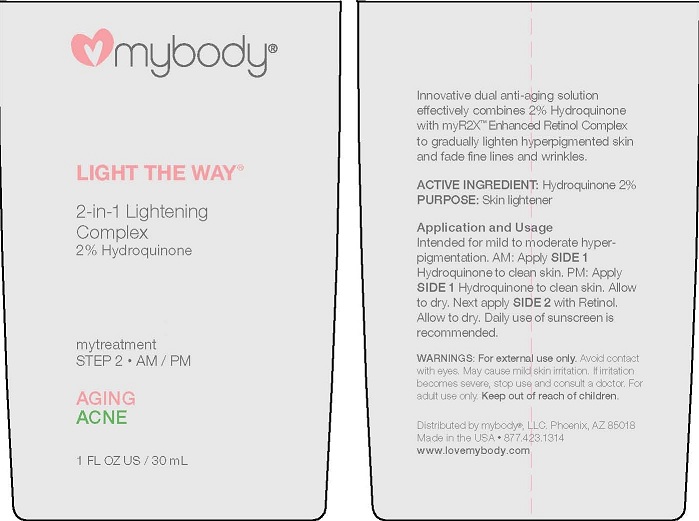 DRUG LABEL: LIGHT THE WAY
NDC: 49520-201 | Form: LOTION
Manufacturer: mybody
Category: otc | Type: HUMAN OTC DRUG LABEL
Date: 20120502

ACTIVE INGREDIENTS: HYDROQUINONE 2 g/100 mL
INACTIVE INGREDIENTS: WATER; HEXYL LAURATE; GLYCERYL STEARATE SE; CETYL ALCOHOL; MEDIUM-CHAIN TRIGLYCERIDES; STEARIC ACID; SHEA BUTTER; GLYCERIN; CETETH-2; DOCOSANOL; HYDROXYPROPYL CORN STARCH (5% SUBSTITUTION BY WEIGHT); XANTHAN GUM; POTASSIUM HYDROXIDE; SODIUM SULFITE; CAPRYLYL GLYCOL; PHENOXYETHANOL; CITRIC ACID MONOHYDRATE; SODIUM METABISULFITE

LIGHT THE WAY

ACTIVE INGREDIENT HYDROQUINONE 2%

PURPOSE SKIN LIGHTENING

INDICATIONS AND USAGE

USE GRADUALLY AND EFFECTIVELY LIGHTENS DARK AREAS IN THE SKIN

WARNINGS

FOR EXTERNAL USE ONLY

DO NOT USE

- ON INFLAMED OR BROKEN SKIN.
- FOR THE PREVENTION OF SUNBURN.
- AS A SUNSCREEN.

ASK A DOCTOR OR PHARMACIST BEFORE USE IF

- PREGNANT OR LACTATING.
- IN COMBINATION WITH PRODUCTS CONTAINING RESORCINOL, PHENOL, OR SALICYLIC ACID.
- BY CHILDREN UNDER THE AGE OF 12.

STOP USE AND ASK A DOCTOR

- IF AREAS DARKEN OR BLUE-BLACK DARKENING OCCURS.
- MILD IRRITATION MAY OCCUR. IF IRRITATION BECOMES SEVERE, STOP USE AND CONSULT A DOCTOR.

KEEP OUT OF REACH OF CHILDREN * IF SWALLOWED, GET MEDICAL HELP OR CONTACT A POISON CONTROL CENTER RIGHT AWAY.

DIRECTIONS

- ADULTS ONLY
- PM: APPLY SIDE 1 HYDROQUINONE TO CLEAN SKIN. ALLOW TO DRY. NEXT APPLY SIDE 2 WITH RETINOL. ALLOW TO DRY. DAILY USE OF SUNSCREEN IS RECOMMENDED.
- FOR BEST RESULTS: APPLY MYBODY'S PROTECT AND SERVE SUN SHIELD SPF 30 (AM ONLY) WHEN USING LIGHT THE WAY.
- FOR SENSITIVE SKIN, TEST OVERNIGHT ON SMALL AREA (INSIDE ELBOW).
- IF NO IMPROVEMENT IS SEEN AFTER 3 MONTHS, DISCONTINUE USE. ON VERY DARK SKIN, LIGHTENING EFFECT MAY NOT BE NOTICEABLE.
- TO PREVENT DARKENING FROM REOCCURRING, USE A SUNSCREEN OR WEAR PROTECTIVE CLOTHING TO COVER TREATED SKIN DURING AND AFTER PRODUCT USE.

OTHER INFORMATION

* AVOID STORAGE AT EXTREME TEMPERATURES (BELOW 40°F AND ABOVE 100°F).

INACTIVE INGREDIENT

INACTIVE INGREDIENTS CHAMBER A: WATER, HEXYL LAURATE, GLYCERYL STEARATE SE, CETYL ALCOHOL, CAPRYLIC/CAPRIC TRIGLYCERIDE, STEARIC ACID, BUTYROSPERMUM PARKII (SHEA BUTTER), GLYCERIN, CETETH-2, BEHENYL ALCOHOL, HYDROXYPROPYL STARCH PHOSPHATE, XANTHAN GUM, POTASSIUM HYDROXIDE, SODIUM SULFITE, FRAGRANCE, CAPRYLYL GLYCOL, PHENOXYETHANOL, CITRIC ACID, SODIUM METABISULFITE.

QUESTIONS OR COMMENTS?

CALL 877.423.1314 * WWW.LOVEMYBODY.COM

PACKAGE LABEL

MYBODY

LIGHT THE WAY

BOOSTER PACK: HYPERPIGMENTATION

MYBOOSTER * STEP 2

WHEN USING THIS PRODUCT

- AVOID CONTACT WITH EYES.
- LIMIT SUN EXPOSURE.